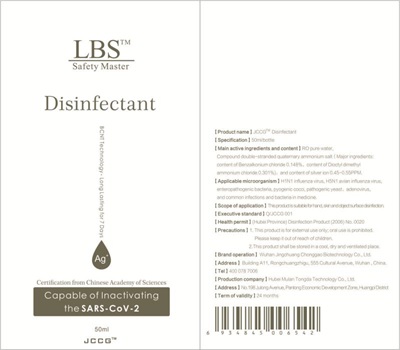 DRUG LABEL: Jingchuang Chonggao Disinfectant
NDC: 81895-101 | Form: SPRAY
Manufacturer: Wuhan Jingchuang Chonggao Biotechnology Co., Ltd.
Category: otc | Type: HUMAN OTC DRUG LABEL
Date: 20210506

ACTIVE INGREDIENTS: BENZALKONIUM CHLORIDE 0.148 g/100 mL
INACTIVE INGREDIENTS: WATER; DIOCTYLDIMONIUM CHLORIDE

Jingchuang Chonggao Disinfectant

Jingchuang Chonggao Disinfectant

Active Ingredient(s)

Dioctyl dimethyl ammonium chloride 0.301g/100mL; Benzalkonium chloride 0.148g/100mL. Purpose: Antiseptic

Purpose

Antiseptic, Jingchuang Chonggao Disinfectant

Use

Jingchuang Chonggao Disinfectant to help reduce bacteria that potentially can cause disease. For use when soap and water are not available.

Warnings

For external use only.

Do not use

- on open skin wounds

When using this product keep out of eyes, ears, and mouth. In case of contact with eyes, rinse eyes thoroughly with water.
Stop use and ask a doctor if irritation or rash occurs. These may be signs of a serious condition.
Keep out of reach of children. If swallowed, get medical help or contact a Poison Control Center right away.

Stop use and ask a doctor if irritation or rash occurs. These may be signs of a serious condition.

Keep out of reach of children. If swallowed, get medical help or contact a Poison Control Center right away.

Directions

- Spray on the skin.
- Supervise children under 6 years of age when using this product to avoid swallowing.

Other information

- Store between 15-30C (59-86F)
- Avoid freezing and excessive heat above 40C (104F)

Inactive ingredients

purified water USP